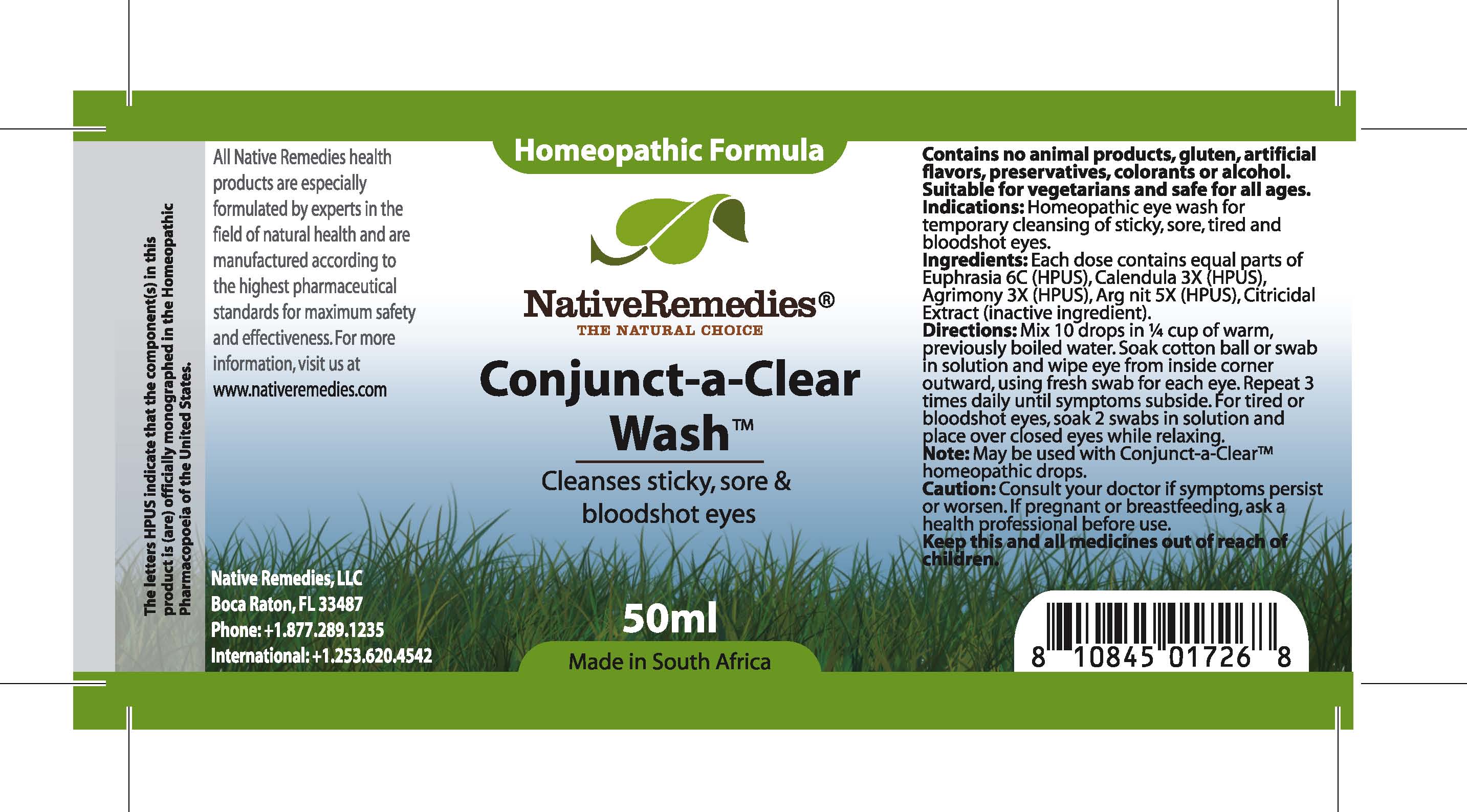 DRUG LABEL: Conjunct-a-Clear Wash
NDC: 68647-174 | Form: TINCTURE
Manufacturer: Feelgood Health
Category: homeopathic | Type: HUMAN OTC DRUG LABEL
Date: 20100726

ACTIVE INGREDIENTS: EUPHRASIA STRICTA 6 [hp_C]/50 mL; CALENDULA OFFICINALIS FLOWER 3 [hp_X]/50 mL; AGRIMONIA EUPATORIA 3 [hp_X]/50 mL; SILVER NITRATE 5 [hp_X]/50 mL
INACTIVE INGREDIENTS: CITRUS PARADISI SEED 0.125 mL/50 mL; WATER 45.038 mL/50 mL

CONJUCT-A-CLEAR WASH

PURPOSE

Cleanses sticky, sore and bloodshot eyes

INDICATIONS AND USAGE

Indications: Homeopathic eye wash for cleansing of sticky, sore, tired and bloodshot eyes.

DOSAGE AND ADMINISTRATION

Directions: Mix 10 drops in ¼ cup of warm, previously boiled water. Soak cotton ball or swab in solution and wipe eye from inside corner outward, using fresh swab for each eye. Repeat 3 times daily until symptoms subside. For tired or bloodshot eyes, soak 2 swabs in solution and place over closed eyes while relaxing. May be used with Conjunct-a-Clear™ homeopathic drops.

GENERAL PRECAUTIONS

Caution: Consult your doctor if symptoms persist or worsen. Keep this and all medicines out of reach of children.

Citricidal Extract (inactive ingredient)

PREGNANCY

If pregnant or breastfeeding, ask a health professional before use.

ACTIVE INGREDIENT

Ingredients: Each dose contains equal parts of Euphrasia (6C) (HPUS), Calendula (3X) (HPUS), Agrimony (3X) (HPUS), Arg nit (5X) (HPUS)

Citricidal Extract (inactive ingredient).

PREGNANCY

If pregnant or breastfeeding, ask a health professional before use.

WARNINGS

Contains no animal products, gluten, artificial flavors, preservatives, colorants or alcohol. Suitable for vegetarians and safe for all ages.

PATIENT COUNSELING INFORMATION

All Native Remedies health products are especially formulated by experts in the field of natural health and are manufactured according to the highest pharmaceutical standards for maximum safety and effectiveness. For more information, visit us at www.nativeremedies.com

Distributed by

Native Remedies, LLC

6531 Park of Commerce Blvd.

Suite 160

Boca Raton, FL 33487

Phone: 1.877.289.1235

International: + 1.561.999.8857

The letters HPUS indicate that the component(s) in this product is (are) officially monographed in the Homeopathic Pharmacopoeia of the United States.

KEEP OUT OF REACH OF CHILDREN

Keep this and all medicines out of reach of children.